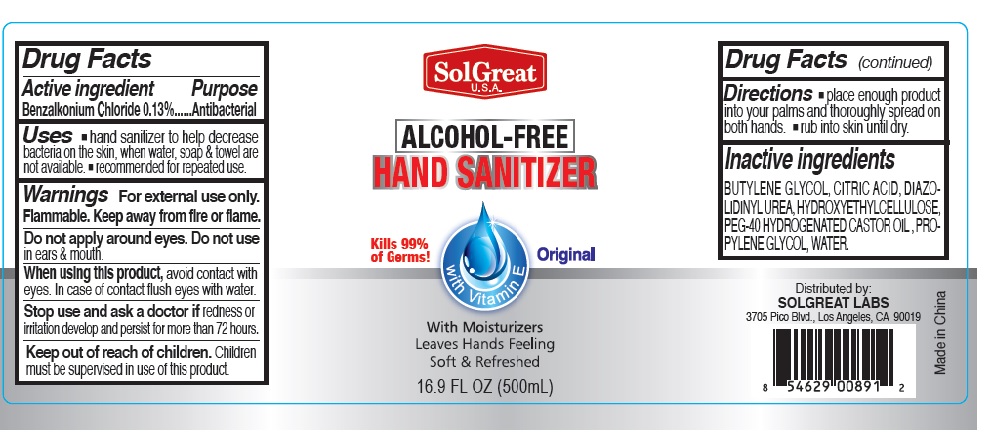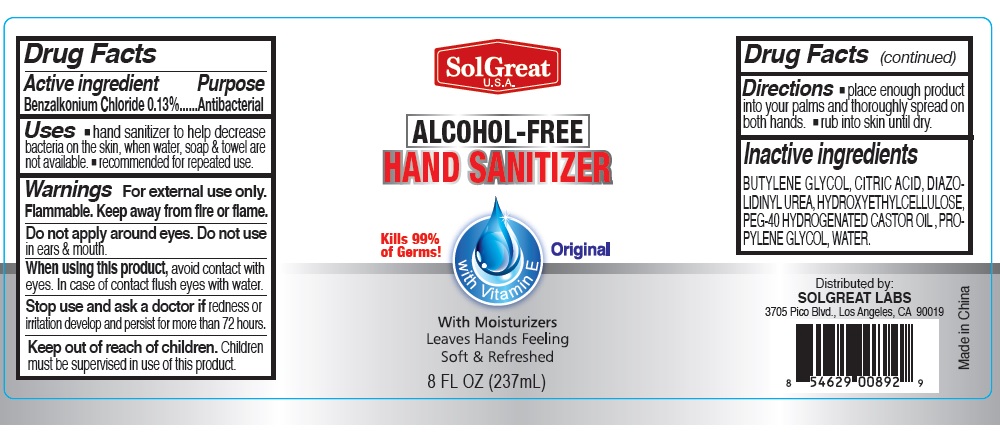 DRUG LABEL: SolGreat Alcohol-Free Hand Sanitizer
NDC: 73913-004 | Form: GEL
Manufacturer: PANATURAL USA, INC.
Category: otc | Type: HUMAN OTC DRUG LABEL
Date: 20200422

ACTIVE INGREDIENTS: Benzalkonium Chloride 1.3 mg/1 mL
INACTIVE INGREDIENTS: BUTYLENE GLYCOL; CITRIC ACID MONOHYDRATE; DIAZOLIDINYL UREA; POLYOXYL 40 HYDROGENATED CASTOR OIL; HYDROXYETHYL CELLULOSE (4000 MPA.S AT 1%); PROPYLENE GLYCOL; WATER

SolGreat Alcohol-Free Hand Sanitizer

Active lngredient

Benzalkonium Chloride

Purpose

Antibacterial

Uses

- hand sanitizer to help decrease bacteria on the skin, when water, soap & towel are not available.
- recommended for repeated use

Warnings

For external use only.

Flammable. Keep away from fire or flame.

Do not apply around eyes. Do not use in ears & mouth.

When using this product, avoid contact with eyes. In case of contact flush eyes with water.

Stop use and ask a doctor if redness or irritation develop and persist for more than 72 hours.

Directions

- place enough product into your palms and thoroughly spread on both hands.
- rub into skin until dry.

Inactive ingredients

BUTYLENE GLYCOL, CITRIC ACID, DIAZOLIDINYL UREA, HYDROXYETHYCELLULOSE, PEG-40 HYDROGENATE CASTOR OIL, PROPYLENE GLYCOL, WATER.

Keep out of reach of children

Children must be supervised in use of this product